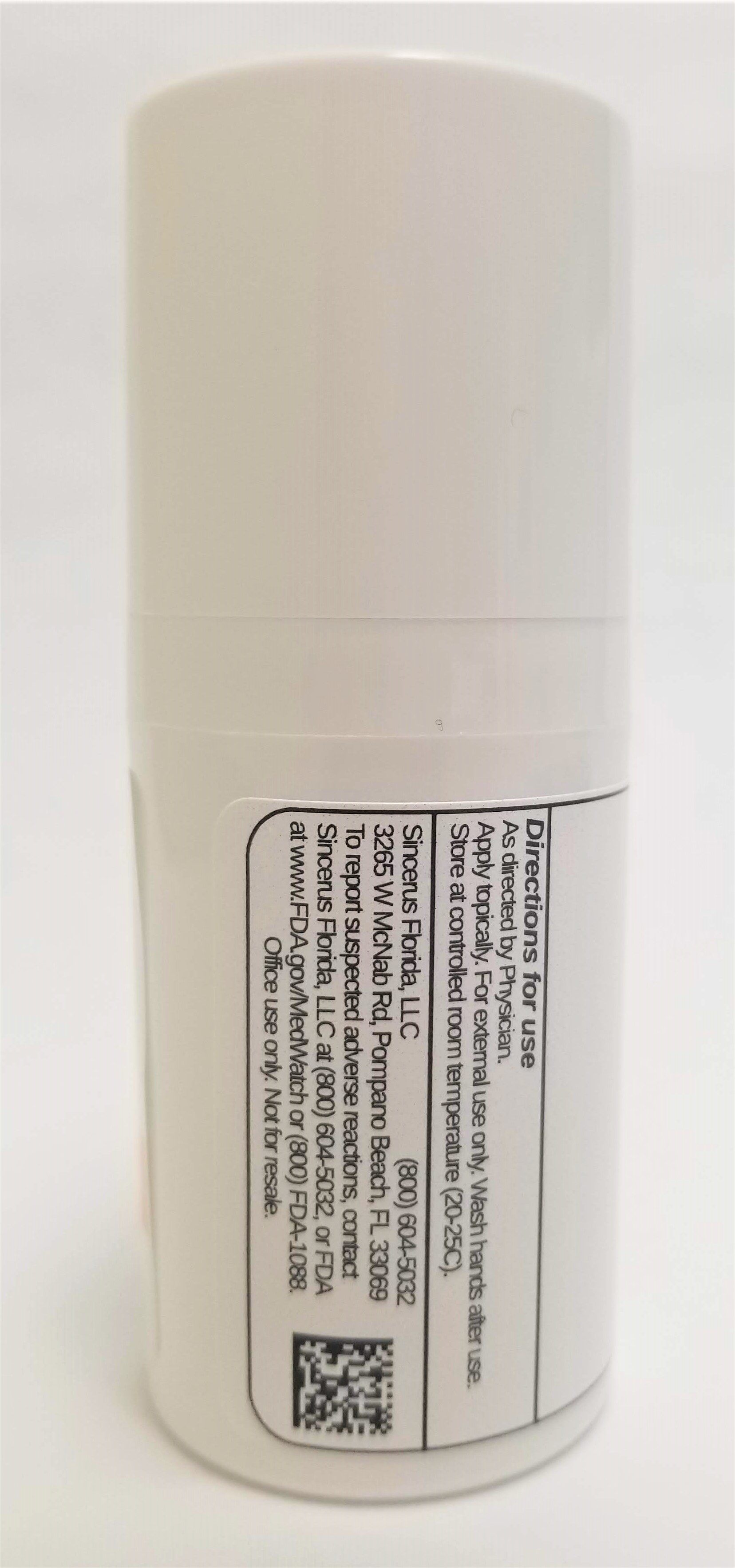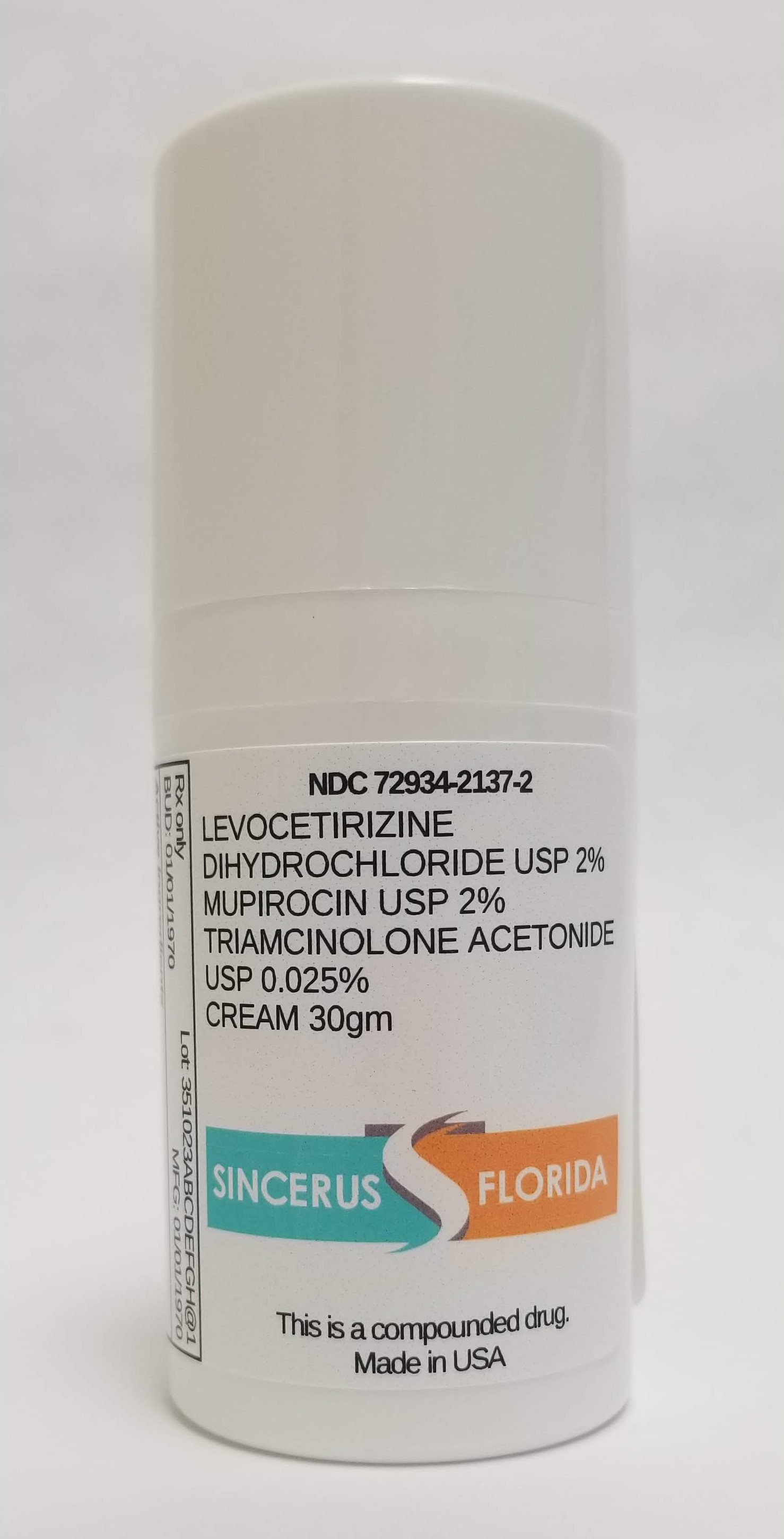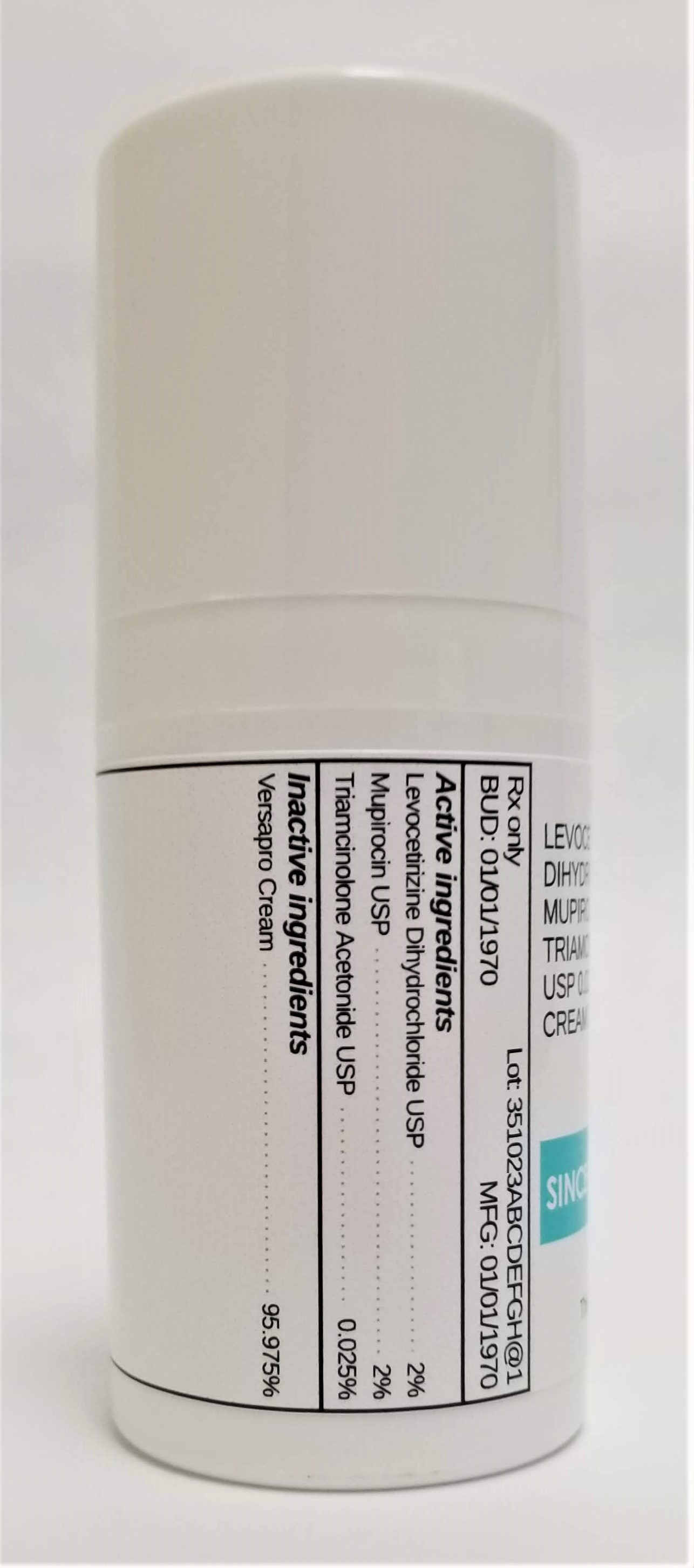 DRUG LABEL: LEVOCETIRIZINE DIHYDROCHLORIDE 2% / MUPIROCIN 2% / TRIAMCINOLONE ACETONIDE 0.025%
NDC: 72934-2137 | Form: CREAM
Manufacturer: Sincerus Florida, LLC
Category: prescription | Type: HUMAN PRESCRIPTION DRUG LABEL
Date: 20190514

ACTIVE INGREDIENTS: LEVOCETIRIZINE DIHYDROCHLORIDE 2 g/100 g; MUPIROCIN 2 g/100 g; TRIAMCINOLONE ACETONIDE 0.025 g/100 g

LEVOCETIRIZINE DIHYDROCHLORIDE 2% / MUPIROCIN 2% / TRIAMCINOLONE ACETONIDE 0.025%